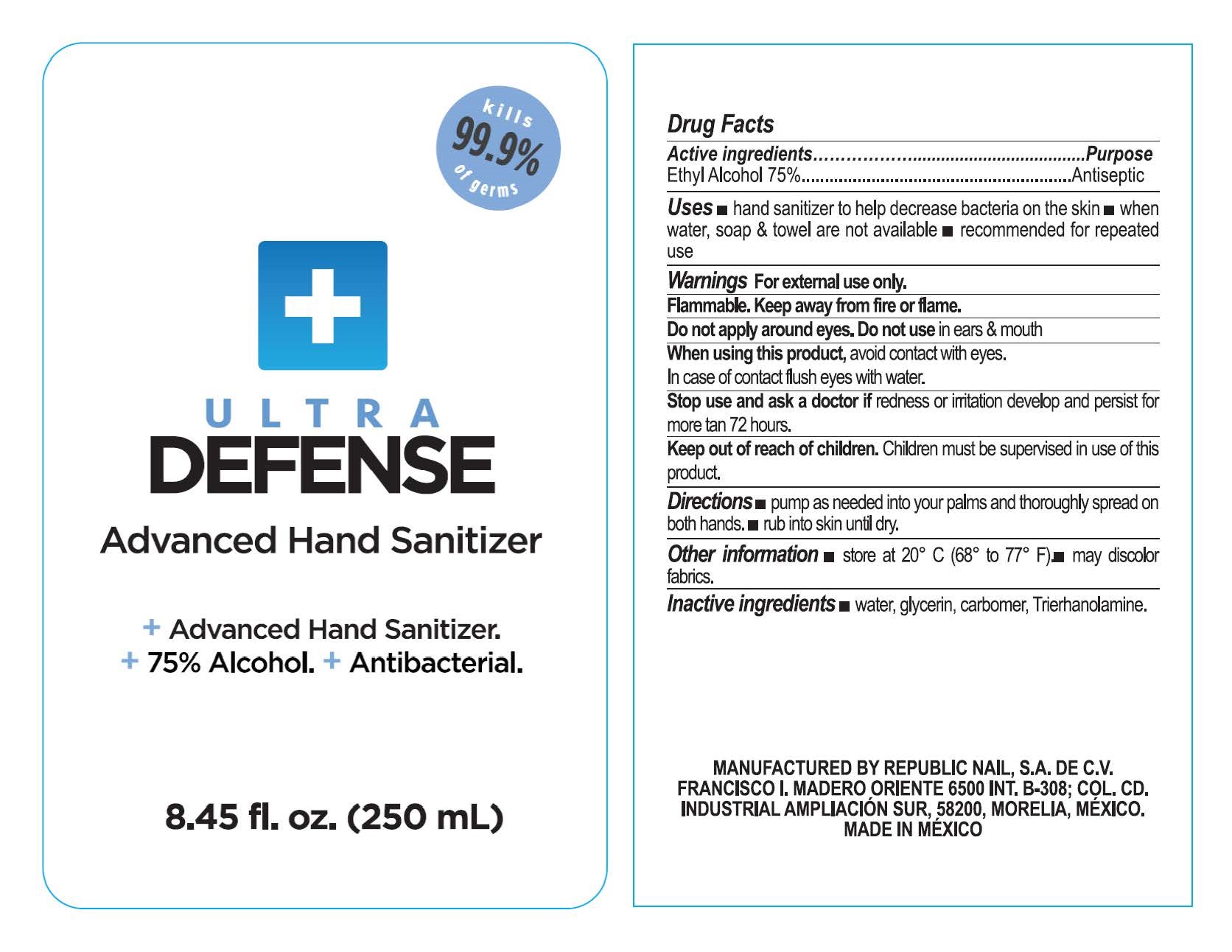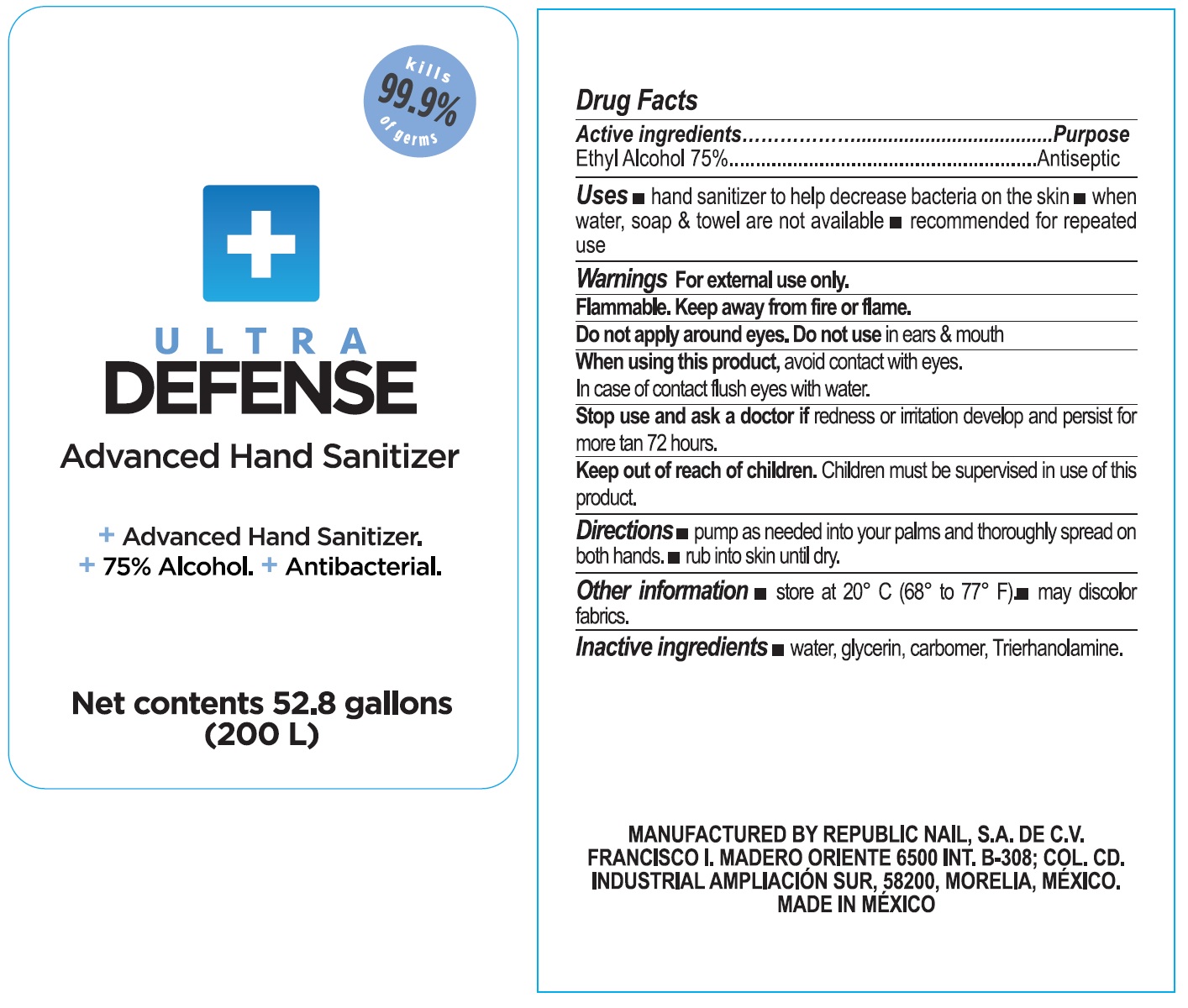 DRUG LABEL: Ultra Defense Advanced Hand Sanitizer
NDC: 77618-001 | Form: GEL
Manufacturer: Republic Nail, S.A. de C.V.
Category: otc | Type: HUMAN OTC DRUG LABEL
Date: 20200601

ACTIVE INGREDIENTS: ALCOHOL 0.75 L/1 L
INACTIVE INGREDIENTS: WATER; GLYCERIN; CARBOMER HOMOPOLYMER, UNSPECIFIED TYPE; TROLAMINE

Ultra Defense Advanced Hand Sanitizer

Active ingredients

Ethyl Alcohol 75%

Purpose

Antiseptic

Uses

- hand sanitizer to help decrease baceteria on the skin
- when water, soap & towel are not available
- recommended for repetaed use

Warnings

For external use only.

Flammable, Keep away from fire or flame.

Do not apply around eyes.

Do not use

in ears & mouth

When using this product,

avoid contact with eyes. In case of contact flush eyes with water.

Stop use and ask a doctor if

redness or irritation develop and persist for more than 72 hours.

Keep out of reach of children.

Children must be supervised in use of this product.

Directions

- pump as needed into your palms and thoroughly spread on both hands.
- rub into skin until dry.

Other informaton

- store at 20° C (68° to 77° F)
- may discolor fabrics.

Inactive ingredients

water, glycerin, carbomer, Treithanolamine.